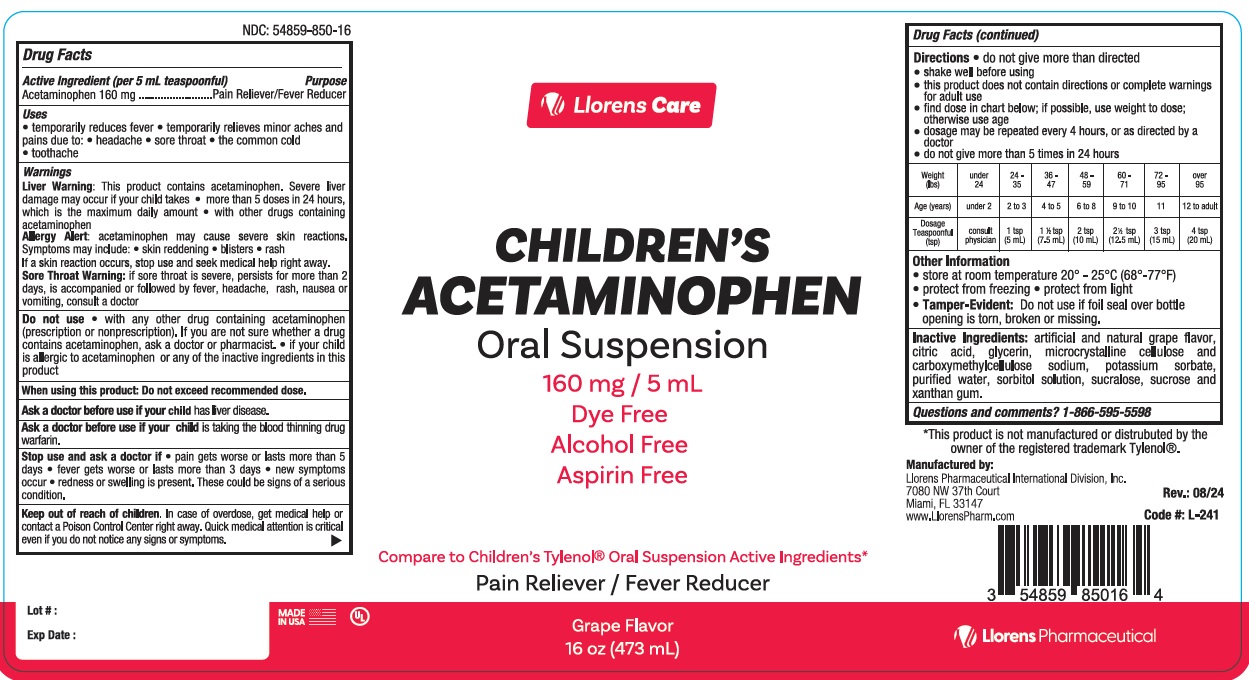 DRUG LABEL: Llorens Care Children Acetaminophen
NDC: 54859-850 | Form: SUSPENSION
Manufacturer: Llorens Pharmaceutical International Division, Inc.
Category: otc | Type: HUMAN OTC DRUG LABEL
Date: 20251231

ACTIVE INGREDIENTS: ACETAMINOPHEN 160 mg/5 mL
INACTIVE INGREDIENTS: SUCROSE; SUCRALOSE; POTASSIUM SORBATE; XANTHAN GUM; GLYCERIN; SODIUM CITRATE; CITRIC ACID MONOHYDRATE; SORBITOL; WATER; MICROCRYSTALLINE CELLULOSE; CARBOXYMETHYLCELLULOSE SODIUM, UNSPECIFIED

Llorens-APAPSusChild 850

Active ingredient (in each 5mL = 1 teaspoon)

Acetaminophen 160 mg

Purpose

Pain Reliever / Fever Reducer

Uses

- temporarily reduces fever
- temporarilty relieves minor aches and pains due to:
- headache
- sore throat
- the common cold
- toothache

Warnings

Liver warning

This product contains acetaminophen. Severe liver damage may occur if your child takes

- more than 5 doses in 24 hours, which is the maximum daily amount
- with other drugs containing acetaminophen.

Allergy Alert:

acetaminophen may cause sever skin reactions. Symptoms may include

- skin reddening
- blisters
- rash

If a skin reaction occurs, stop use and seek medical help right away.

Sore throat warning

if sore throat is severe, persists for more than 2 days, is accompanied or followed by fever, headache, rash, nausea, or vomiting, consult a doctor promptly.

Do not use

- with any other drug containing acetaminophen (prescription or non-prescription). If you are not sure whether a drug contains acetaminophen, ask a doctor or pharmacist.
- if your child is allergic to acetaminophen or any of the inactive ingredients in this product.

When using this product: Do not exceed recommended dose.

Ask a doctor before use if your child hasliver disease.

Ask a doctor or pharmacist before use if your child istaking the blood thinning drug warfarin.

Stop use and ask a doctor if

- pain gets worse or lasts more than 5 days
- fever gets worse or lasts more than 3 days
- new symptoms occur
- redness or swelling is present. These could be signs of a serious condition.

Keep out of reach of children.

Overdose warning

Taking more than the recommended dose (overdose) may cause liver damage. In case of overdose, get medical help or contact a Poison Control Center right away. Quick medical attention is critical even if you do not notice any signs or symptoms.

Directions

- do not give more than directed
- shake well before using
- this product does not contain directions or complete warnings for adult use
- find dose in chart below; if possible, use weight to dose, otherwise use age
- dosage may be repeated every 4 hours, or as directed by a doctor
- do not give more than 5 times in 24 hours

Weight (lbs) | under 24 | 24-35 | 36-47 | 48-59 | 60-71 | 72-95 | over 95
Age (years) | under 2 | 2 to 3 | 4 to 5 | 6 to 8 | 9 to 10 | 11 | 12 to adult
Dosage Teaspoonful (tsp) | consult physician | 1 tsp (5 mL) | 1 1/2 tsp (7.5 mL) | 2 tsp (10 mL) | 2 1/2 tsp (12.5 mL) | 3 tsp (15 mL) | 4 tsp (20 (mL)

Inactive ingredients

artifical and natural grap flavor, citric acid, glycerin, microcrystalline cellulose and carboxymethylcellulose, sodium, potassium sorbate, purified water, sorbitol solution, sucralose, and xanthan gum

QUESTIONS? COMMENTS?

Call 1-866-595-5598